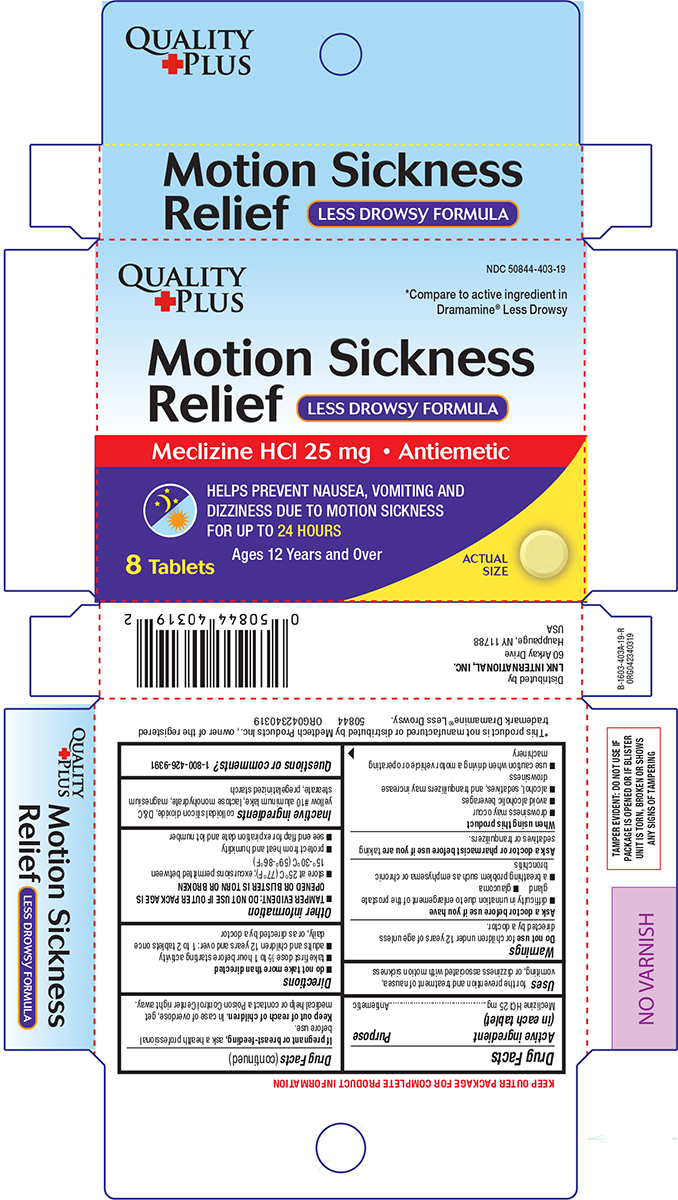 DRUG LABEL: Motion Sickness Relief
NDC: 50844-403 | Form: TABLET
Manufacturer: L.N.K. International, Inc.
Category: otc | Type: HUMAN OTC DRUG LABEL
Date: 20250719

ACTIVE INGREDIENTS: MECLIZINE HYDROCHLORIDE 25 mg/1 1
INACTIVE INGREDIENTS: SILICON DIOXIDE; D&C YELLOW NO. 10 ALUMINUM LAKE; LACTOSE MONOHYDRATE; MAGNESIUM STEARATE; STARCH, CORN

Quality Plus 44-403A

Active ingredient (in each tablet)

Meclizine HCl 25 mg

Purpose

Antiemetic

Uses

for the prevention and treatment of nausea, vomiting, or dizziness associated with motion sickness

Warnings

Do not use

for children under 12 years of age unless directed by a doctor.

Ask a doctor before use if you have

- difficulty in urination due to enlargement of the prostate gland
- glaucoma
- a breathing problem such as emphysema or chronic bronchitis

Ask a doctor or pharmacist before use if you are

taking sedatives or tranquilizers.

When using this product

- drowsiness may occur
- avoid alcoholic beverages
- alcohol, sedatives, and tranquilizers may increase drowsiness
- use caution when driving a motor vehicle or operating machinery

If pregnant or breast-feeding,

ask a health professional before use.

Keep out of reach of children.

In case of overdose, get medical help or contact a Poison Control Center right away.

Directions

- do not take more than directed
- take first dose ½ to 1 hour before starting activity
- adults and children 12 years and over: 1 to 2 tablets once daily, or as directed by a doctor

Other information

- TAMPER EVIDENT: DO NOT USE IF OUTER PACKAGE IS OPENED OR BLISTER IS TORN OR BROKEN
- store at 25ºC (77ºF); excursions permitted between 15º-30ºC (59º-86ºF)
- protect from heat and humidity
- see end flap for expiration date and lot number

Inactive ingredients

colloidal silicon dioxide, D&C yellow #10 aluminum lake, lactose monohydrate, magnesium stearate, pregelatinized starch

Questions or comments?

1-800-426-9391

Principal Display Panel

QUALITY
+PLUS

NDC 50844-403-19

*Compare to active ingredient in
Dramamine® Less Drowsy

Motion Sickness
Relief
LESS DROWSY FORMULA
Meclizine HCl 25 mg • Antiemetic

HELPS PREVENT NAUSEA, VOMITING AND
DIZZINESS DUE TO MOTION SICKNESS
FOR UP TO 24 HOURS

Ages 12 Years and Over

8 Tablets

ACTUAL
SIZE

TAMPER EVIDENT: DO NOT USE IF
PACKAGE IS OPENED OR IF BLISTER
UNIT IS TORN, BROKEN OR SHOWS
ANY SIGNS OF TAMPERING

*This product is not manufactured or distributed by Medtech Products Inc., owner of the registered trademark
Dramamine® All Day Less Drowsy. 50844 ORG042340319

Distributed by
LNK INTERNATIONAL, INC.
60 Arkay Drive
Hauppauge, NY 11788
USA

Quality Plus 44-403A